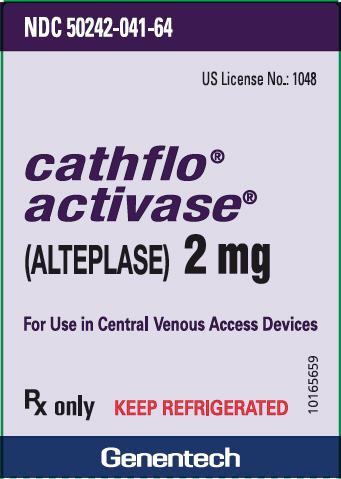 DRUG LABEL: Cathflo Activase
NDC: 50242-041 | Form: INJECTION, POWDER, LYOPHILIZED, FOR SOLUTION
Manufacturer: Genentech, Inc.
Category: prescription | Type: HUMAN PRESCRIPTION DRUG LABEL
Date: 20260120

ACTIVE INGREDIENTS: ALTEPLASE 2.2 mg/2 mL
INACTIVE INGREDIENTS: ARGININE 77 mg/2 mL; POLYSORBATE 80 0.2 mg/2 mL; PHOSPHORIC ACID

Cathflo® Activase®
(Alteplase)

Powder for reconstitution for use in central venous access devices

DESCRIPTION

Cathflo® Activase® (Alteplase) is a tissue plasminogen activator (t‑PA) produced by recombinant DNA technology. It is a sterile, purified glycoprotein of 527 amino acids. It is synthesized using the complementary DNA (cDNA) for natural human tissue‑type plasminogen activator (t‑PA) obtained from an established human cell line. The manufacturing process involves secretion of the enzyme Alteplase into the culture medium by an established mammalian cell line (Chinese hamster ovary cells) into which the cDNA for Alteplase has been genetically inserted.

Cathflo Activase (Alteplase) for injection is a sterile, white to pale yellow, lyophilized powder for intracatheter instillation for restoration of function to central venous access devices following reconstitution with Sterile Water for Injection, USP.

Each vial of Cathflo Activase contains 2.2 mg of Alteplase (which includes a 10% overfill), 77 mg of L‑arginine, 0.2 mg of polysorbate 80, and phosphoric acid for pH adjustment. Each reconstituted vial will deliver 2 mg of Cathflo Activase, at a pH of approximately 7.3.

CLINICAL PHARMACOLOGY

Alteplase is an enzyme (serine protease) that has the property of fibrin-enhanced conversion of plasminogen to plasmin. It produces limited conversion of plasminogen in the absence of fibrin. Alteplase binds to fibrin in a thrombus and converts the entrapped plasminogen to plasmin, thereby initiating local fibrinolysis (1).

In patients with acute myocardial infarction administered 100 mg of Activase as an accelerated intravenous infusion over 90 minutes, plasma clearance occurred with an initial half‑life of less than 5 minutes and a terminal half‑life of 72 minutes. Clearance is mediated primarily by the liver (2).

When Cathflo Activase is administered for restoration of function to central venous access devices according to the instructions in DOSAGE AND ADMINISTRATION, circulating plasma levels of Alteplase are not expected to reach pharmacologic concentrations. If a 2 mg dose of Alteplase were administered by bolus injection directly into the systemic circulation (rather than instilled into the catheter), the concentration of circulating Alteplase would be expected to return to endogenous circulating levels of 5–10 ng/mL within 30 minutes (1).

CLINICAL STUDIES

Three clinical studies were performed in patients with improperly functioning central venous access devices (CVADs).

A placebo‑controlled, double‑blind, randomized trial (Trial 1) and a larger open‑label trial (Trial 2) investigated the use of Alteplase in predominately adult patients who had an indwelling CVAD for administration of chemotherapy, total parenteral nutrition, or long‑term administration of antibiotics or other medications. Both studies enrolled patients whose catheters were not functioning (defined as the inability to withdraw at least 3 mL of blood from the device) but had the ability to instill the necessary volume of study drug. Patients with hemodialysis catheters or a known mechanical occlusion were excluded from both studies. Also excluded were patients considered at high risk for bleeding or embolization (see PRECAUTIONS, Bleeding), as well as patients who were younger than 2 years old or weighed less than 10 kg. Restoration of function was assessed by successful withdrawal of 3 mL of blood and infusion of 5 mL of saline through the catheter.

Trial 1 tested the efficacy of a 2 mg/2 mL Alteplase dose in restoring function to occluded catheters in 150 patients with catheter occlusion up to 24 hours in duration. Patients were randomized to receive either Alteplase or placebo instilled into the lumen of the catheter, and catheter function was assessed at 120 minutes. Restoration of function was assessed by successful withdrawal of 3 mL of blood and infusion of 5 mL of saline through the catheter. All patients whose catheters did not meet these criteria were then administered Alteplase, until function was restored or each patient had received up to two active doses. After the initial dose of study agent, 51 (67%) of 76 patients randomized to Alteplase and 12 (16%) of 74 patients randomized to placebo had catheter function restored. This resulted in a treatment‑associated difference of 51% (95% CI is 37% to 64%). A total of 112 (88%) of 127 Alteplase‑treated patients had restored function after up to two doses.

Trial 2 was an open‑label, single arm trial in 995 patients with catheter dysfunction and included patients with occlusions present for any duration. Patients were treated with Alteplase with up to two doses of 2 mg/2 mL (less for children who weighed less than 30 kg, see DOSAGE AND ADMINISTRATION) instilled into the lumen of the catheter. Assessment for restoration of function was made at 30 minutes after each instillation. If function was not restored, catheter function was re‑assessed at 120 minutes. Thirty minutes after instillation of the first dose, 516 (52%) of 995 patients had restored catheter function. One hundred twenty minutes after the instillation of the first dose, 747 (75%) of 995 patients had restored catheter function. If function was not restored after the first dose, a second dose was administered. Two hundred nine patients received a second dose. Thirty minutes after instillation of the second dose, 70 (33%) of 209 patients had restored catheter function. One hundred twenty minutes after the instillation of the second dose, 97 (46%) of 209 patients had restored catheter function. A total of 844 (85%) of 995 patients had function restored after up to 2 doses.

Across Trials 1 and 2, 796 (68%) of 1043 patients with occlusions present for less than 14 days had restored function after one dose, and 902 (88%) had function restored after up to two doses. Of 53 patients with occlusions present for longer than 14 days, 30 (57%) patients had function restored after a single dose, and a total of 38 patients (72%) had restored function after up to two doses.

Three hundred forty-six patients who had successful treatment outcome were evaluated at 30 days after treatment. The incidence of recurrent catheter dysfunction within this period was 26%.

Trial 3 was an open‑label, single‑arm trial in 310 patients between the ages of 2 weeks and 17 years. All patients had catheter dysfunction defined as the inability to withdraw blood (at least 3 mL for patients ≥ 10 kg or at least 1 mL for patients < 10 kg). Catheter dysfunction could be present for any duration. The indwelling CVADs (single-, double-, and triple‑lumen, and implanted ports) were used for administration of chemotherapy, blood products or fluid replacement, total parenteral nutrition, antibiotics, or other medications. Patients with hemodialysis catheters or known mechanical occlusions were excluded from the study, as were patients considered at high risk for bleeding or embolization. Patients were treated with up to two doses of Cathflo Activase instilled into the catheter lumen. For patients weighing ≥ 30 kg, the dose was 2 mg in 2 mL. For patients weighing < 30 kg, the dose was 110% of the estimated internal lumen volume, not to exceed 2 mg in 2 mL. Restoration of function was assessed at 30 and 120 minutes (if required) after administration of each dose. Restoration of function was defined as the ability to withdraw fluid (3 mL in patients ≥ 10 kg; 1 mL in patients < 10 kg) and infuse saline (5 mL in patients ≥ 10 kg; 3 mL in patients < 10 kg).

The overall rate of catheter function restoration of 83% (257 of 310) was similar to that observed in Trial 2, as were the rates of function restoration at the intermediate assessments.

The three trials had similar rates of catheter function restoration among the catheter types studied (single-, double-, and triple‑lumen, and implanted ports). No gender differences were observed in the rate of catheter function restoration. Results were similar across all age subgroups.

INDICATIONS AND USAGE

Cathflo® Activase® (Alteplase) is indicated for the restoration of function to central venous access devices as assessed by the ability to withdraw blood.

CONTRAINDICATIONS

Cathflo Activase should not be administered to patients with known hypersensitivity to Alteplase or any component of the formulation (see DESCRIPTION).

WARNINGS

None.

PRECAUTIONS

General

Catheter dysfunction may be caused by a variety of conditions other than thrombus formation, such as catheter malposition, mechanical failure, constriction by a suture, and lipid deposits or drug precipitates within the catheter lumen. These types of conditions should be considered before treatment with Cathflo Activase.

Because of the risk of damage to the vascular wall or collapse of soft‑walled catheters, vigorous suction should not be applied during attempts to determine catheter occlusion.

Excessive pressure should be avoided when Cathflo Activase is instilled into the catheter. Such force could cause rupture of the catheter or expulsion of the clot into the circulation.

Bleeding

The most frequent adverse reaction associated with all thrombolytics in all approved indications is bleeding (3,4). Cathflo Activase has not been studied in patients known to be at risk for bleeding events that may be associated with the use of thrombolytics. Caution should be exercised with patients who have active internal bleeding or who have had any of the following within 48 hours: surgery, obstetrical delivery, percutaneous biopsy of viscera or deep tissues, or puncture of non‑compressible vessels. In addition, caution should be exercised with patients who have thrombocytopenia, other hemostatic defects (including those secondary to severe hepatic or renal disease), or any condition for which bleeding constitutes a significant hazard or would be particularly difficult to manage because of its location, or who are at high risk for embolic complications (e.g., venous thrombosis in the region of the catheter). Death and permanent disability have been reported in patients who have experienced stroke and other serious bleeding episodes when receiving pharmacologic doses of a thrombolytic.

Should serious bleeding in a critical location (e.g., intracranial, gastrointestinal, retroperitoneal, pericardial) occur, treatment with Cathflo Activase should be stopped and the drug should be withdrawn from the catheter.

Infections

Cathflo Activase should be used with caution in the presence of known or suspected infection in the catheter. Using Cathflo Activase in patients with infected catheters may release a localized infection into the systemic circulation (see ADVERSE REACTIONS). As with all catheterization procedures, care should be used to maintain aseptic technique.

Hypersensitivity

Hypersensitivity, including urticaria, angioedema and anaphylaxis, has been reported in association with use of Cathflo Activase. Monitor patients treated with Cathflo Activase for signs of hypersensitivity and treat appropriately if necessary.

Re-Administration

In clinical trials, patients received up to two 2 mg/2 mL doses (4 mg total) of Alteplase. Additional re-administration of Cathflo Activase has not been studied. Antibody formation in patients receiving one or more doses of Cathflo Activase for restoration of function to CVADs has not been studied.

Drug Interactions

The interaction of Cathflo Activase with other drugs has not been formally studied. Concomitant use of drugs affecting coagulation and/or platelet function has not been studied.

Drug/Laboratory Test Interactions

Potential interactions between Cathflo Activase and laboratory tests have not been studied.

Carcinogenesis, Mutagenesis, Impairment of Fertility

Long‑term studies in animals have not been performed to evaluate the carcinogenic potential or the effect on fertility. Short-term studies that evaluated tumorigenicity of Alteplase and effect on tumor metastases were negative in rodents. Studies to determine mutagenicity (Ames test) and chromosomal aberration assays in human lymphocytes were negative at all concentrations tested. Cytotoxicity, as reflected by a decrease in mitotic index, was evidenced only after prolonged exposure at high concentrations exceeding those expected to be achieved with Cathflo Activase.

Pregnancy

Alteplase has been shown to have an embryocidal effect due to an increased postimplantation loss rate in rabbits when administered intravenously during organogenesis at a dose (3 mg/kg) approximately 50 times human exposure (based on AUC) at the dose for restoration of function to occluded CVADs. No maternal or fetal toxicity was evident at a dose (1 mg/kg) approximately 16 times human exposure at the dose for restoration of function to occluded CVADs.

There are no adequate and well‑controlled studies in pregnant women. Cathflo Activase should be used during pregnancy only if the potential benefit justifies the potential risk to the fetus.

Nursing Mothers

It is not known whether Cathflo Activase is excreted in human milk. Because many drugs are excreted in human milk, caution should be exercised when Cathflo Activase is administered to a nursing woman.

Pediatric Use

A total of 432 subjects under age 17 have received Cathflo Activase in the three trials. Rates of serious adverse events were similar in the pediatric and adult patients, as were the rates of catheter function restoration.

Geriatric Use

In 312 patients enrolled who were age 65 years and over, no incidents of intracranial hemorrhage (ICH), embolic events, or major bleeding events were observed. One hundred three of these patients were age 75 years and over, and 12 were age 85 years and over. The effect of Alteplase on common age-related comorbidities has not been studied. In general, caution should be used in geriatric patients with conditions known to increase the risk of bleeding (see PRECAUTIONS, Bleeding).

ADVERSE REACTIONS

The following adverse reactions are discussed in greater detail in Section PRECAUTIONS of the label:

- Bleeding
- Hypersensitivity

In the clinical trials, the most serious adverse events reported after treatment were sepsis (see PRECAUTIONS, Infections), gastrointestinal bleeding, and venous thrombosis.

Because clinical trials are conducted under widely varying conditions, adverse reaction rates observed in the clinical trials of a drug cannot be directly compared to rates in the clinical trials of another drug and may not reflect the rates observed in practice.

Trials 1 and 2

The data described for Trials 1 and 2 reflect exposure to Cathflo Activase in 1122 patients, of whom 880 received a single dose and 242 received two sequential doses of Cathflo Activase.

In the Cathflo Activase Trials 1 and 2, only limited, focused types of serious adverse events were recorded, including death, major hemorrhage, intracranial hemorrhage, pulmonary or arterial emboli, and other serious adverse events not thought to be attributed to underlying disease or concurrent illness. Major hemorrhage was defined as severe blood loss (> 5 mL/kg), blood loss requiring transfusion, or blood loss causing hypotension. Non‑serious adverse events and serious events thought to be due to underlying disease or concurrent illness were not recorded. Patients were observed for serious adverse events until catheter function was deemed to be restored or for a maximum of 4 or 6 hours depending on study. For most patients the observation period was 30 minutes to 2 hours. Spontaneously reported deaths and serious adverse events that were not thought to be related to the patient's underlying disease were also recorded during the 30 days following treatment.

Four catheter-related sepsis events occurred from 15 minutes to 1 day after treatment with Alteplase, and a fifth sepsis event occurred on Day 3 after Alteplase treatment. All 5 patients had positive catheter or peripheral blood cultures within 24 hours after symptom onset.

Three patients had a major hemorrhage from a gastrointestinal source from 2 to 3 days after Alteplase treatment. One case of injection site hemorrhage was observed at 4 hours after treatment in a patient with pre-existing thrombocytopenia. These events may have been related to underlying disease and treatments for malignancy, but a contribution to occurrence of the events from Alteplase cannot be ruled out. There were no reports of intracranial hemorrhage.

Three cases of subclavian and upper extremity deep venous thrombosis were reported 3 to 7 days after treatment. These events may have been related to underlying disease or to the long-term presence of an indwelling catheter, but a contribution to occurrence of the events from Alteplase treatment cannot be ruled out. There were no reports of pulmonary emboli.

There were no gender-related differences observed in the rates of adverse reactions. Adverse reactions profiles were similar across all age subgroups.

Trial 3

In Trial 3 all serious adverse events were recorded with a specific interest in intracranial hemorrhage, major hemorrhage, thrombosis, embolic events, sepsis and catheter related complications. Major hemorrhage was defined as severe blood loss (> 5 mL/kg), blood loss requiring transfusion, or blood loss causing hypotension. Non-serious adverse events were not recorded. Patients were observed until catheter function was deemed to be restored or for a maximum of 4 hours after the first dose. Additionally, serious adverse events were elicited from patients at 48 hours (up to 96 hours) following completion of treatment.

No pediatric patients in Trial 3 experienced an intracranial hemorrhage, major hemorrhage, thrombosis, or an embolic event.

Three cases of sepsis occurred 2 to 44 hours after treatment with Cathflo Activase. All of these patients had evidence of infection prior to administration of Cathflo Activase. An additional patient developed fever and lethargy within one day of Cathflo Activase administration, which required outpatient intravenous antibiotics. In one subject, the lumen of the catheter, placed 2 years previously, ruptured with infusion of the study drug.

There were no gender-related differences observed in the rates of adverse reactions. Adverse reactions profiles were similar across all age groups.

DOSAGE AND ADMINISTRATION

Cathflo® Activase® (Alteplase) is for instillation into the dysfunctional catheter at a concentration of 1 mg/mL.

• Patients weighing ≥30 kg: | 2 mg in 2 mL
• Patients weighing <30 kg: | 110% of the internal lumen volume of the catheter, not to exceed 2 mg in 2 mL

If catheter function is not restored at 120 minutes after 1 dose of Cathflo Activase, a second dose may be instilled (see Instructions for Administration). There is no efficacy or safety information on dosing in excess of 2 mg per dose for this indication. Studies have not been performed with administration of total doses greater than 4 mg (two 2‑mg doses).

Instructions for Administration

Preparation of Solution

Reconstitute Cathflo Activase to a final concentration of 1 mg/mL:

1. Aseptically withdraw 2.2 mL of Sterile Water for Injection, USP (diluent is not provided). Do not use Bacteriostatic Water for Injection.
2. Inject the 2.2 mL of Sterile Water for Injection, USP, into the Cathflo Activase vial, directing the diluent stream into the powder. Slight foaming is not unusual; let the vial stand undisturbed to allow large bubbles to dissipate.
3. Mix by gently swirling until the contents are completely dissolved. Complete dissolution should occur within 3 minutes. DO NOT SHAKE. The reconstituted preparation results in a colorless to pale yellow transparent solution containing 1 mg/mL Cathflo Activase at a pH of approximately 7.3.
4. Cathflo Activase contains no antibacterial preservatives and should be reconstituted immediately before use. The solution may be used for intracatheter instillation within 8 hours following reconstitution when stored at 2–30°C (36–86°F).

No other medication should be added to solutions containing Cathflo Activase.

Instillation of Solution into the Catheter

1. Inspect the product prior to administration for foreign matter and discoloration.
2. Withdraw 2 mL (2 mg) of solution from the reconstituted vial.
3. Instill the appropriate dose of Cathflo Activase (see DOSAGE AND ADMINISTRATION) into the occluded catheter.
4. After 30 minutes of dwell time, assess catheter function by attempting to aspirate blood. If the catheter is functional, go to Step 7. If the catheter is not functional, go to Step 5.
5. After 120 minutes of dwell time, assess catheter function by attempting to aspirate blood and catheter contents. If the catheter is functional, go to Step 7. If the catheter is not functional, go to Step 6.
6. If catheter function is not restored after one dose of Cathflo Activase, a second dose of equal amount may be instilled. Repeat the procedure beginning with Step 1 under Preparation of Solution.
7. If catheter function has been restored, aspirate 4–5 mL of blood in patients ≥10 kg or 3 mL in patients <10 kg to remove Cathflo Activase and residual clot, and gently irrigate the catheter with 0.9% Sodium Chloride Injection, USP.

Any unused solution should be discarded.

Stability and Storage

Store lyophilized Cathflo Activase at refrigerated temperature (2–8°C/36–46°F). Do not use beyond the expiration date on the vial. Protect the lyophilized material during extended storage from excessive exposure to light.

HOW SUPPLIED

Cathflo Activase (Alteplase) for injection is supplied as a sterile, lyophilized powder in 2 mg vials.

Cathflo®Activase® is available in a carton that contains one 2 mg vial of Cathflo® Activase® (Alteplase): NDC 50242‑041‑64 or a carton that contains ten 2 mg vials of Cathflo® Activase® (Alteplase): NDC 50242-041-10.

REFERENCES

1. Collen D, Lijnen HR. Fibrinolysis and the control of hemostasis. In: Stamatoyannopoulos G, Nienhui AW, Majerus PW, Varmus H, editors. The molecular basis of blood diseases, 2nd edition. Philadelphia: Saunders, 1994:662–88.
2. Tanswell P, Tebbe U, Neuhaus K-L, Glasle-Schwarz L, Wojick J, Seifried E. Pharmacokinetics and fibrin specificity of alteplase during accelerated infusions in acute myocardial infarction. J Am Coll Cardiol 1992;19:1071–5.
3. Califf RM, Topol EJ, George BS, Boswick JM, Abbottsmith C, Sigmon KN, et al., and the Thrombolysis and Angioplasty in Myocardial Infarction Study Group. Hemorrhagic complications associated with the use of intravenous tissue plasminogen activator in treatment of acute myocardial infarction. Am J Med 1988;85:353–9.
4. Bovill EG, Terrin ML, Stump DC, Berke AD, Frederick M, Collen D, et al. Hemorrhagic events during therapy with recombinant tissue-type plasminogen activator, heparin, and aspirin for acute myocardial infarction: results of the thrombolysis in myocardial infarction (TIMI), phase II trial. Ann Int Med 1991;115:256–65.

Cathflo® Activase®
(Alteplase)
Manufactured by: Genentech, Inc. A Member of the Roche Group 1 DNA Way South San Francisco, CA 94080-4990 US License No. 1048 | FDA Approval Date January 2005 Revised: 02/2019 Cathflo® Activase® is a trademark of Genentech, Inc. ©2019 Genentech, Inc.

Representative sample of labeling (see the HOW SUPPLIED section for complete listing):

PRINCIPAL DISPLAY PANEL - 2 mg Vial Carton

NDC 50242-041-64

US License No.: 1048

cathflo®
activase®
(ALTEPLASE) 2 mg

For Use in Central Venous Access Devices

Rx only
KEEP REFRIGERATED

10165659

Genentech